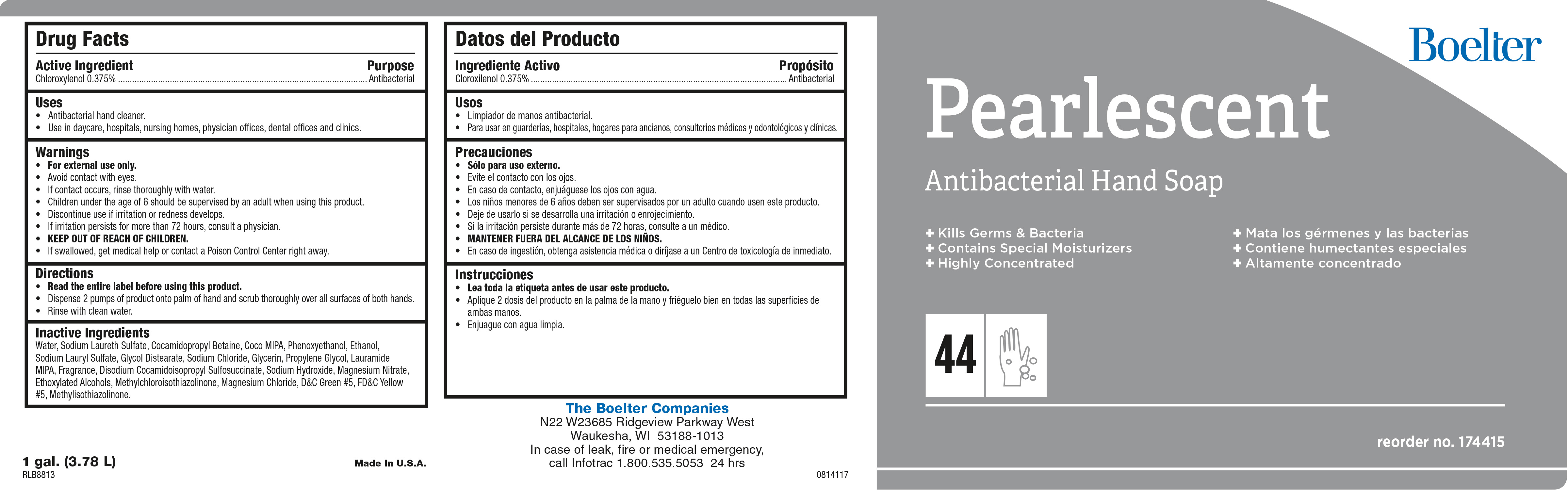 DRUG LABEL: Pearlescent
NDC: 57468-708 | Form: SOAP
Manufacturer: Boelter Companies Inc.
Category: otc | Type: HUMAN OTC DRUG LABEL
Date: 20200729

ACTIVE INGREDIENTS: CHLOROXYLENOL 3.75 mg/1 mL
INACTIVE INGREDIENTS: WATER; COCO DIETHANOLAMIDE; COCAMIDOPROPYL BETAINE; PHENOXYETHANOL; PROPYLENE GLYCOL; MYRCENE; LAURIC DIETHANOLAMIDE; TRIBASIC CALCIUM PHOSPHATE; D&C GREEN NO. 5; FD&C YELLOW NO. 5; CALCIUM SILICATE; SODIUM LAURYL SULFATE; DIMETHYL BENZYL CARBINYL BUTYRATE; BENZYL BENZOATE; DIOXANE; SODIUM HYDROXIDE; METHYLISOTHIAZOLINONE; METHYL ALCOHOL; .GAMMA.-DECALACTONE; MAGNESIUM NITRATE; SODIUM ALUMINIUM SILICATE; SODIUM FERROCYANIDE; ETHYL ACETOACETATE; LAURIC ISOPROPANOLAMIDE; DIMETHYL BENZYL CARBINYL ACETATE; SODIUM CARBONATE; GLYCOL DISTEARATE; METHYL ANTHRANILATE; METHYLCHLOROISOTHIAZOLINONE; ETHYL METHYLPHENYLGLYCIDATE; ETHYL BUTYRATE; ETHYLENE OXIDE; CHLOROACETIC ACID; LINALOOL, (+/-)-

Pearlescent

Pearlescent

Active Ingredient

Chloroxylenol 0.375%

Pearlescent

Uses

- Antibacterial hand cleaner.
- Use in daycare, hospitals, nursing homes, physicians offices, dental offices and clinics

Pearlescent

Warnings

- For external use only.
- Avoid contact with eyes.
- Children under the age of 6 should be supervised by an adult when using this product.
- Discontinue use is irritation or redness develops.
- If irritation persists for more than 72 hours, consult a physician.
- KEEP OUT OF REACH OF CHILDREN.

Pearlescent

Directions

- Read the entire label before using this product.
- Dispense 1-2 pumps of product onto wet palm.
- Lather and rinse hands with clean water

Pearlescent

Inactive Ingredients

Water, Sodium Lauryl lSulfate, Cocamide DEA, Cocamidopropyl betadine, Phenoxyethanol, Sodium Laureth Sulfate, Propylene Glycol, Fragrance, DMDM Hydantoin, Glycol Stearate, Laurimide DEA, Glycerine, Tocopheryl Acetate, D&C Green #5, FD&C Yellow #5.

Pearlescent

Purpose

Antibacterial

Pearlescent

KEEP OUT OF REACH OF CHILDREN